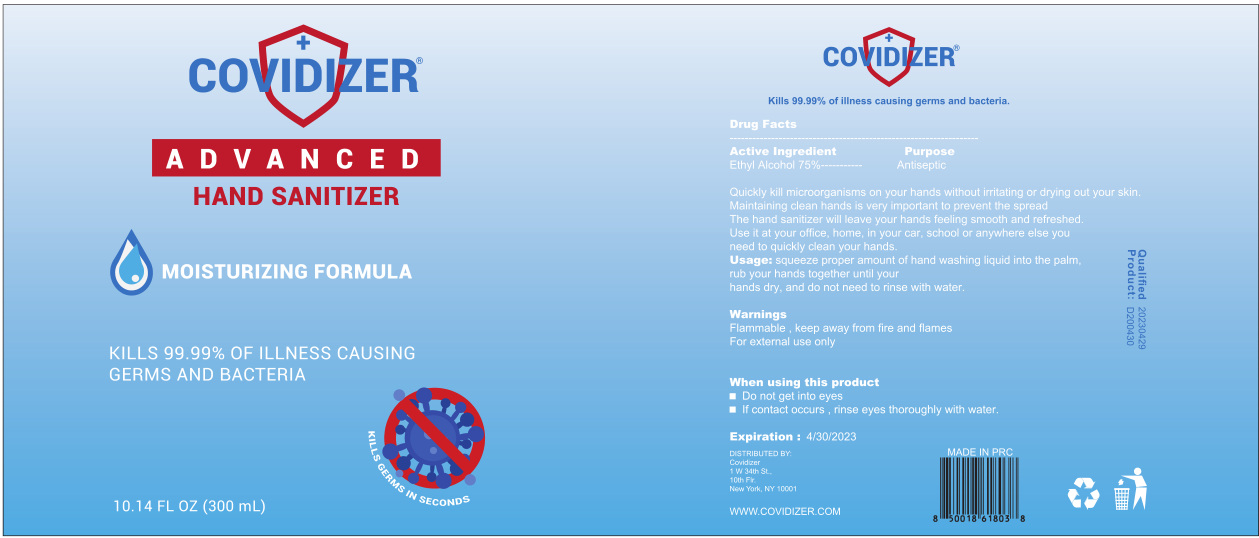 DRUG LABEL: hand sanitizer
NDC: 54493-006 | Form: LIQUID
Manufacturer: Shenzhen YJD Technology Co., Ltd.
Category: otc | Type: HUMAN OTC DRUG LABEL
Date: 20200527

ACTIVE INGREDIENTS: ALCOHOL 225 mL/300 mL
INACTIVE INGREDIENTS: CARBOMER HOMOPOLYMER, UNSPECIFIED TYPE; GLYCERIN; TROLAMINE; WATER

DOSAGE AND ADMINISTRATION

Store in a cool and dry place

INACTIVE INGREDIENT

Water；Glycerin； Carbomer；Triethanolamine

INDICATIONS AND USAGE

squeeze proper amount of hand washing liquid into the palm,rub your hands together until your hands dry, and do not need to rinse with water.

ACTIVE INGREDIENT

Alcohol

keep out of reach of children

PURPOSE

Disinfection
Sterilization
No Rinseing

WARNINGS

Flammable，keep away from fire and flames.For external use only